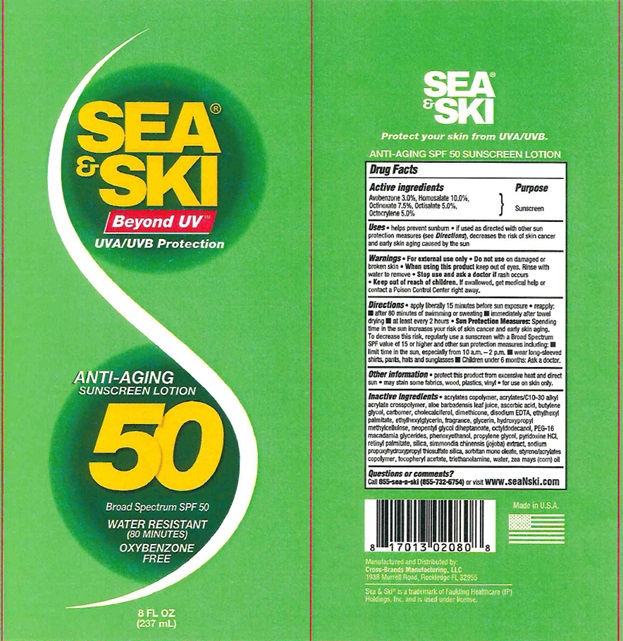 DRUG LABEL: Sea and Ski SPF 50
NDC: 73440-2080 | Form: LOTION
Manufacturer: Cross-Brands Contract Filling
Category: otc | Type: HUMAN OTC DRUG LABEL
Date: 20220805

ACTIVE INGREDIENTS: OCTOCRYLENE 11.85 g/237 g; AVOBENZONE 7.11 g/237 g; HOMOSALATE 23.7 g/237 g; OCTINOXATE 17.78 g/237 g; OCTISALATE 7.11 g/237 g
INACTIVE INGREDIENTS: WATER 116.84 g/237 g

Sea & Ski SPF 50 Lotion